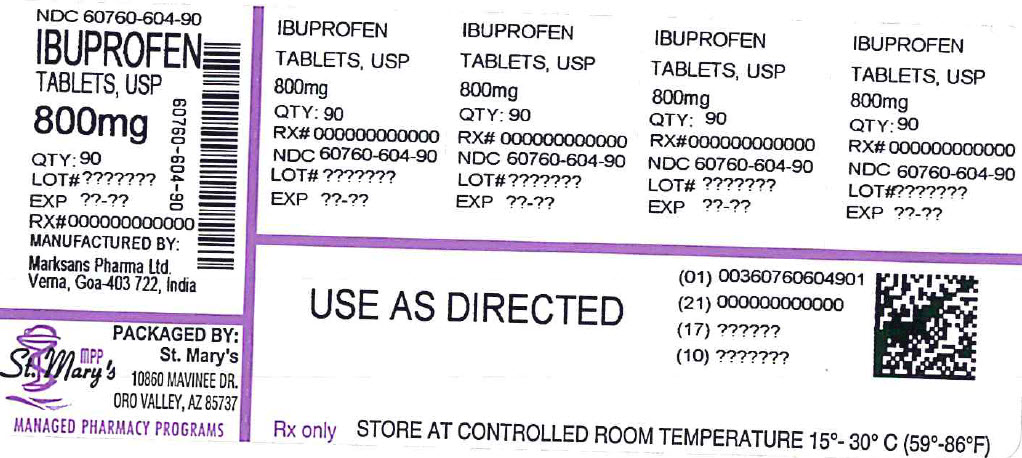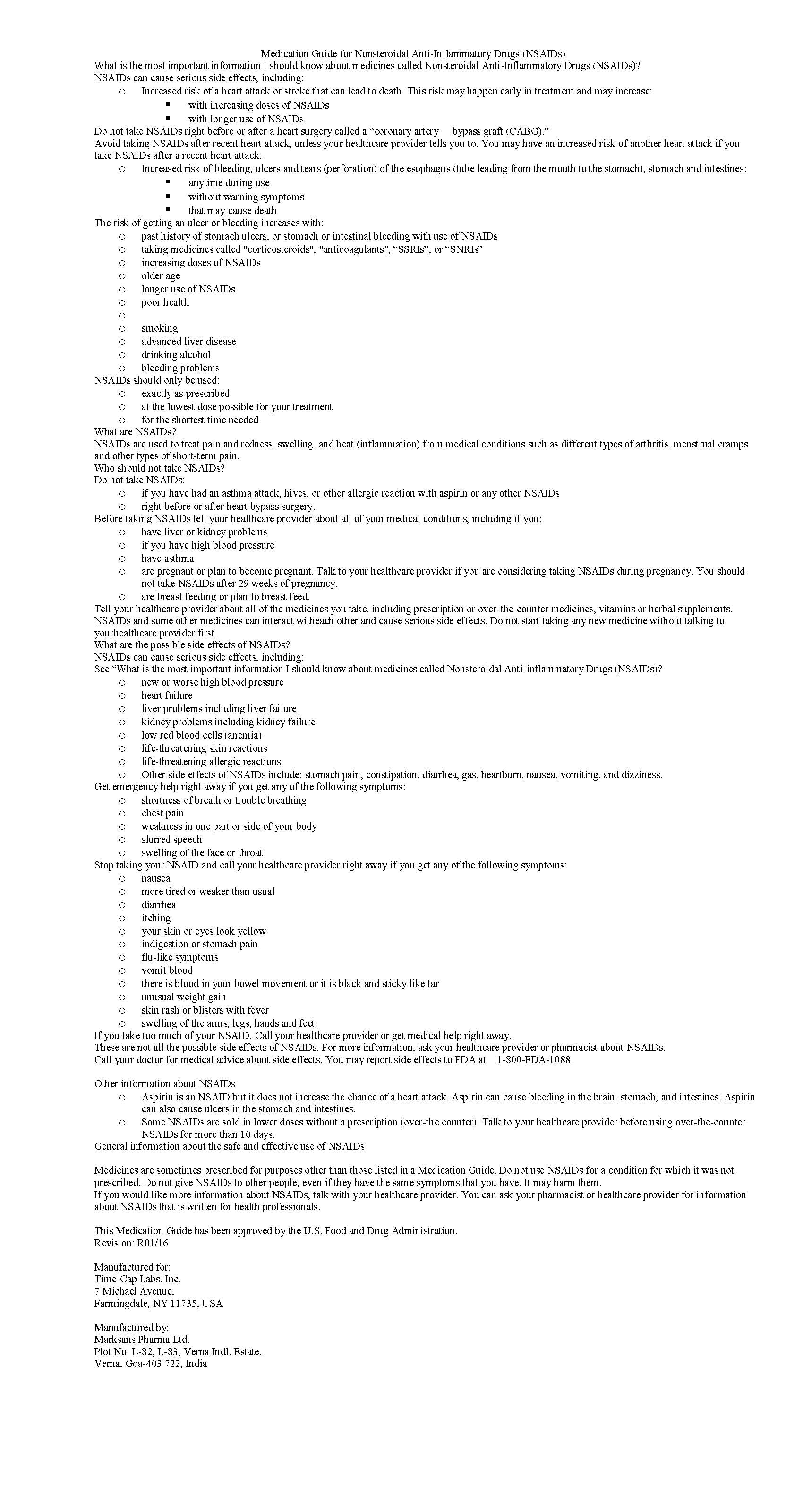 DRUG LABEL: IBUPROFEN
NDC: 60760-604 | Form: TABLET, FILM COATED
Manufacturer: St. Mary's Medical Park Pharmacy
Category: prescription | Type: HUMAN PRESCRIPTION DRUG LABEL
Date: 20241213

ACTIVE INGREDIENTS: IBUPROFEN 800 mg/1 1
INACTIVE INGREDIENTS: SILICON DIOXIDE; CROSCARMELLOSE SODIUM; MAGNESIUM STEARATE; CELLULOSE, MICROCRYSTALLINE; POLYETHYLENE GLYCOL, UNSPECIFIED; POLYVINYL ALCOHOL; STARCH, PREGELATINIZED CORN; TALC; TITANIUM DIOXIDE

IBUPROFEN 400 MG - 600 MG AND 800 MG TABLETS

HOW SUPPLIED

800 mg (white to off-white, capsule shaped, biconvex, film-coated tablets debossed with ‘123’ on one side and plain on other side)

Supplied as:

NDC 60760-604-09 BOTTLES OF 9

NDC 60760-604-20 BOTTLES OF 20

NDC 60760-604-30 BOTTLES OF 30

NDC 60760-604-60 BOTTLES OF 60

NDC 60760-604-90 BOTTLES OF 90